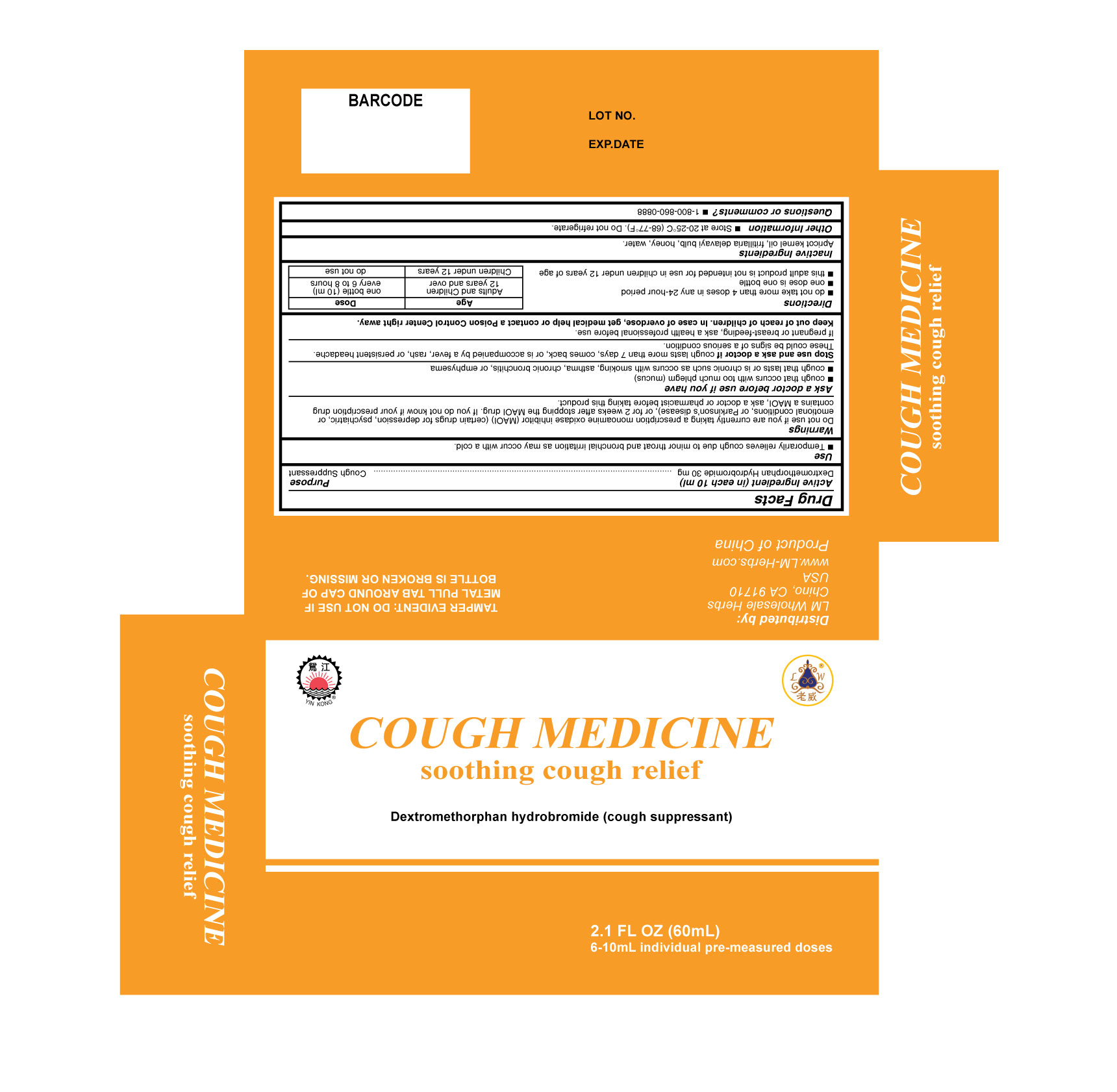 DRUG LABEL: COUGH MEDICINE
NDC: 76206-002 | Form: LIQUID
Manufacturer: RFX Pharmaceutical Co., Ltd.
Category: otc | Type: HUMAN OTC DRUG LABEL
Date: 20200529

ACTIVE INGREDIENTS: DEXTROMETHORPHAN HYDROBROMIDE 30 mg/10 mL
INACTIVE INGREDIENTS: APRICOT KERNEL OIL; HONEY; FRITILLARIA DELAVAYI BULB; WATER

Drug Facts

Active ingredient (in each 10 ml)

Dextromethorphan Hydrobromide, USP 30 mg

Purpose

Cough suppressant

Use

■ Temporarily relieves cough due to minor throat and bronchial irritation as may occur with a cold

Warnings

Do not use if you are now taking a prescription monoamine oxidase inhibitor (MAOI) (certain drugs for depression, psychiatric, or emotional conditions, or Parkinson's disease), or for 2 weeks after stopping the MAOI drug. If you do not know if your prescription drug contains an MAOI, ask a doctor or pharmacist before taking this product.

Ask a doctor before use if you have

■cough that occurs with too much phlegm (mucus)

■cough that lasts or is chronic such as occurs with smoking, asthma, chronic bronchitis or emphysema

Stop use and ask a doctor if

if cough lasts more than 7 days, comes back, or is accompanied by fever, rash, or persistent headache. These could be signs of a serious condition.

If pregnant or breast-feeding

ask a health professional before

Keep out of reach of children

In case of overdose, get medical help or contact a Poison Control Center right away.

Directions

■ do not take more than 4 doses in any 24-hour period

■ one dose is one bottle

■ this adult product is not intended for use in children under 12 years of age

Age Dose

Adults and Children one bottle (10 ml)

12 years and over every 6-8 hours

Children under 12 years do not use

Inactive ingredients

Apricot kernel oil, fritillaria delavayi bulb, honey, water

Other information

■ store at 20-25ºC (68F-77ºF). Do not refrigerate

Questions or comments?

■ 1-800-860-0888